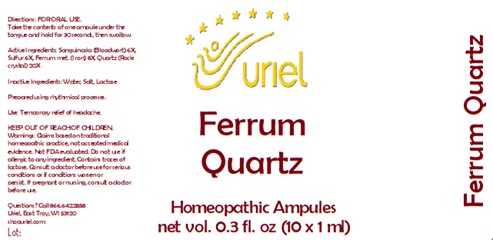 DRUG LABEL: Ferrum Quartz
NDC: 48951-4062 | Form: LIQUID
Manufacturer: Uriel Pharmacy Inc.
Category: homeopathic | Type: HUMAN OTC DRUG LABEL
Date: 20241211

ACTIVE INGREDIENTS: SANGUINARIA CANADENSIS ROOT 6 [hp_X]/1 mL; SULFUR 6 [hp_X]/1 mL; IRON 8 [hp_X]/1 mL; SILICON DIOXIDE 20 [hp_X]/1 mL
INACTIVE INGREDIENTS: WATER; SODIUM CHLORIDE; LACTOSE

Ferrum Quartz

INDICATIONS AND USAGE

Directions: FOR ORAL USE ONLY.

DOSAGE AND ADMINISTRATION

Take the contents of one ampule
under the tongue and hold for
30 seconds, then swallow.

ACTIVE INGREDIENT

Active Ingredients: Sanguinaria (Bloodwort) 6X, Sulfur 6X, Ferrum met. (Iron) 8X, Quartz (Rock crystal) 20X

Inactive Ingredients: Water, Salt, Lactose

Prepared using rhythmical processes.

PURPOSE

Use: Temporary relief of headache.

KEEP OUT OF REACH OF CHILDREN.

WARNINGS

Warnings: Claims based on traditional homeopathic practice, not accepted medical evidence. Not FDA evaluated. Do not use if allergic to any ingredient. Contains traces of lactose. Consult a doctor before use for serious conditions or if conditions worsen or
persist. If pregnant or nursing, consult a doctor before use.

Questions? Call 866.642.2858
Uriel, East Troy, WI 53120
shopuriel.com Lot: